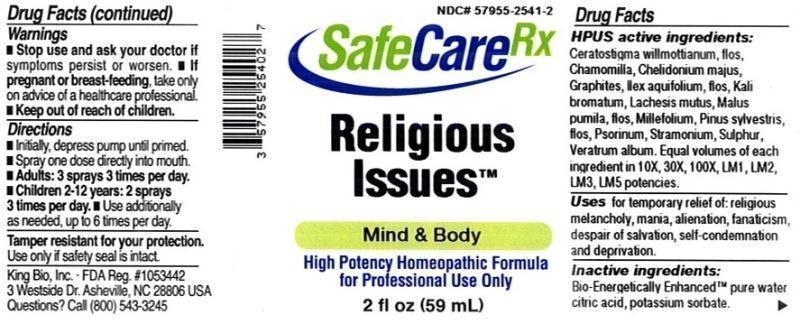 DRUG LABEL: Religious Issues
NDC: 57955-2541 | Form: LIQUID
Manufacturer: King Bio Inc.
Category: homeopathic | Type: HUMAN OTC DRUG LABEL
Date: 20150810

ACTIVE INGREDIENTS: CERATOSTIGMA WILLMOTTIANUM FLOWER 10 [hp_X]/59 mL; MATRICARIA RECUTITA 10 [hp_X]/59 mL; CHELIDONIUM MAJUS 10 [hp_X]/59 mL; GRAPHITE 10 [hp_X]/59 mL; ILEX AQUIFOLIUM FLOWERING TOP 10 [hp_X]/59 mL; POTASSIUM BROMIDE 10 [hp_X]/59 mL; LACHESIS MUTA VENOM 10 [hp_X]/59 mL; MALUS DOMESTICA FLOWER 10 [hp_X]/59 mL; ACHILLEA MILLEFOLIUM 10 [hp_X]/59 mL; PINUS SYLVESTRIS FLOWERING TOP 10 [hp_X]/59 mL; SCABIES LESION LYSATE (HUMAN) 10 [hp_X]/59 mL; DATURA STRAMONIUM 10 [hp_X]/59 mL; SULFUR 10 [hp_X]/59 mL; VERATRUM ALBUM ROOT 10 [hp_X]/59 mL
INACTIVE INGREDIENTS: WATER; ANHYDROUS CITRIC ACID; POTASSIUM SORBATE

Religious Issues

ACTIVE INGREDIENT

Drug Facts__________________________________________________________________________________________________________

HPUS active ingredients: Ceratostigma willmottianum, flos, Chamomilla, Chelidonium majus, Graphites, Ilex aquifolium, flos, Kali bromatum, Lachesis mutus, Malus pumila, flos, Millefolium, Pinus sylvestris, flos, Psorinum, Stramonium, Sulphur, Veratrum album. Equal volumes of each ingredient in 10X, 30X, 100X, LM1, LM2, LM3, LM5 potencies.

INDICATIONS AND USAGE

Uses for temporary relief of: religious melancholy, mania, alienation, fanaticism, despair of salvation, self-condemnation and deprivation.

Inactive Ingredients:

Bio-Energetically Enhanced™ pure water, citric acid and potassium sorbate.

Warnings

- Stop use and ask your doctor if symptoms persist or worsen.
- If pregnant or breast-feeding, take only on advice of a healthcare professional.

- Keep out of reach of children.

Directions

- Initially, depress pump until primed.
- Spray one dose directly into mouth.
- Adults: 3 sprays 3 times per day.
- Children 2-12: 2 sprays 3 times per day.
- Use additionally as needed, up to 6 times per day.

OTHER SAFETY INFORMATION

Tamper resistant for your protection. Use only if seal is intact.

PURPOSE

Uses for temporary relief of:

- religious melancholy
- mania
- alienation
- fanaticism
- despair of salvation
- self-condemnation
- deprivation